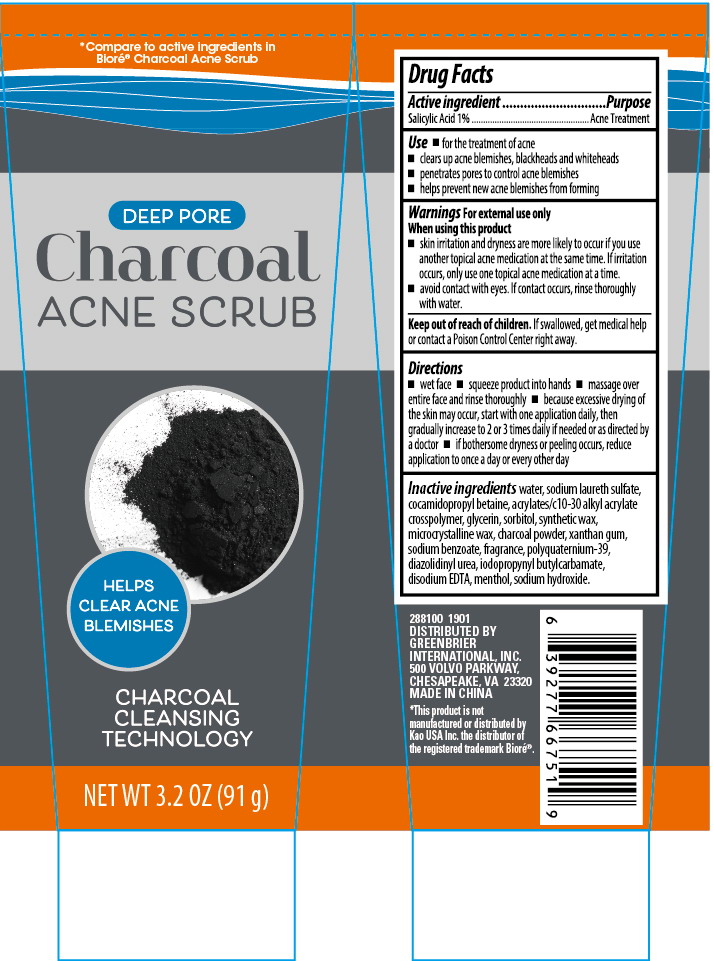 DRUG LABEL: Charcoal Acne Scrub
NDC: 33992-3036 | Form: GEL
Manufacturer: Greenbrier International Inc.
Category: otc | Type: HUMAN OTC DRUG LABEL
Date: 20181217

ACTIVE INGREDIENTS: SALICYLIC ACID 1 g/100 g
INACTIVE INGREDIENTS: WATER; GLYCERIN; COCAMIDOPROPYL BETAINE; CITRIC ACID MONOHYDRATE; ALOE VERA LEAF; SORBITOL; DISODIUM EDTA-COPPER; SODIUM BENZOATE; BUTYL ACRYLATE/METHYL METHACRYLATE/METHACRYLIC ACID COPOLYMER (18000 MW); ACTIVATED CHARCOAL; XANTHAN GUM; SYNTHETIC WAX (1200 MW); MICROCRYSTALLINE WAX; DIAZOLIDINYL UREA; IODOPROPYNYL BUTYLCARBAMATE; MENTHOL; SODIUM HYDROXIDE; POLYQUATERNIUM-39 (22.5/51/26.5 ACRYLIC ACID/ACRYLAMIDE/DADMAC; 1600000 MW)

Charcoal Acne Scrub 3.2 oz

Purpose

Acne treatment

Active Ingredient

Salicylic Acid 1%

Directions

- Wet face
- Squeeze product into hands
- Massage over entire face and rinse thoroughly
- Because excessive drying of the skin may occur, start with one application daily, then gradually increase to 2 to 3 times daily if needed or as directly by a doctor
- If bothersome dryness or peeling occurs, reduce application to once a day or every other day

Keep out of reach of children

If swallowed get medical help or contact a poison control center right away.

INACTIVE INGREDIENT

WATER, SODIUM LAURETH SULFATE, COCAMIDOPROPYL BETAINE, ACRYLATES/C10-30 ALKYL ACRYLATE CROSSPOLYMER, GLYCERIN, SORBITOL, SYNTHETIC WAX, MICROCRYSTALLINE WAX, CHARCOAL POWDER, XANTHAN GUM, SODIUM BENZOATE, FRAGRANCE, POLYQUATERNIUM-39, DIAZOLIDINYL UREA, IODOPROPYNYL BUTYLCARBAMATE, DISODIUM EDTA, MENTHOL, SODIUM HYDROXIDE

Warnings

For external use only

When using this product

- Skin irritation and dryness are more likely to occur if you use another topical acne medication at the same time. If irritation occurs, oinly use one topical acne medication at a time.
- Avoid contact with eyes. If contact occurs, rinse thoroughly with water

Use

- For the treatment of acne
- Clears up acne blemishes, blackheads and whiteheads
- Penetrates pores to control acne blemishes
- Helps prevent new acne blemishes from forming